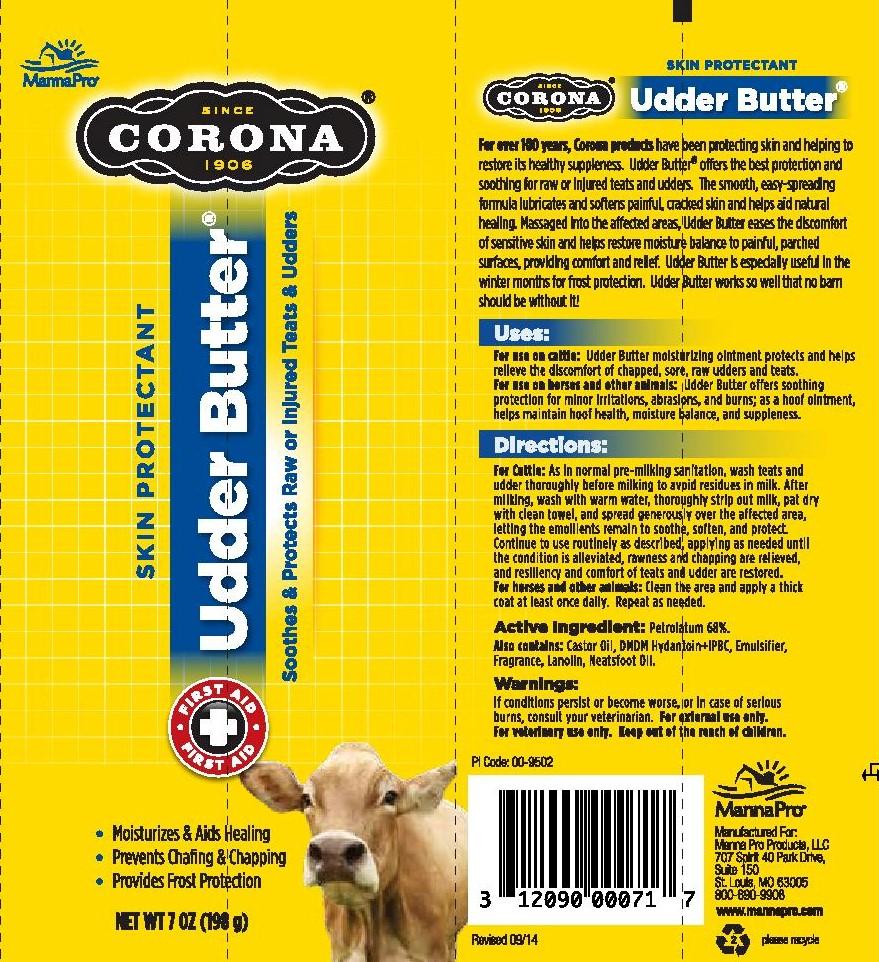 DRUG LABEL: CORONA UDDER BUTTER
NDC: 86077-0321 | Form: OINTMENT
Manufacturer: Manna Pro Products LLC
Category: animal | Type: OTC ANIMAL DRUG LABEL
Date: 20251217

ACTIVE INGREDIENTS: PETROLATUM 68 g/100 g

CORONA UDDER BUTTER

Active Ingredient: Petrolatum 68%

PURPOSE

Corona Udder Butter is a lanolin-enriched moisturizing ointment formulated to protect and help relieve the discomfort of chapped, sore, raw udder and teats.

INDICATIONS AND USAGE

For use on cattle: Udder Butter moisturizing ointment protects and helps relieve the discomfort of chapped, sore, raw udder and teats.

For use on horses and other animals: Udder Butter offers soothing protection for minor irritations, abrasions, and burns, as a hoof ointment, helps maintain hoof health, moisture balance, and suppleness

DOSAGE AND ADMINISTRATION

For Cattle: As in normal pre-milking sanitation, wash teats and udder thoroughly before milking to avoid residues in milk. After milking, wash with warm water, throughly strip out milk, pat dry with clean towel and spread Udder Butter generously over the affected area, letting the emollients remain to soothe, soften and protect.

Continue to use routinely as described, applying as needed until condition is alleviated, rawness and chapping are relieved, resiliency and comfort of teats and udder are restored.

DESCRIPTION

For over 100 years, Corona products have been protecting skin and helping to restore its healthy suppleness. Udder Butter offers the best protection and soothing for raw or injured teats and udders. The smooth, easy-spreading formula lubricates and painful, cracked skin and helps aid natural healing. Massaged into the affected areas, Udder Butter eases the discomfort of sensitive skin and helps restore moisture balance to painful, parched surfaces, providing comfort and relief. Udder is especially useful in the winter months for frost protection. Udder Butter works so well that no barn should be without it!

INACTIVE INGREDIENT

Castor Oil, DMDM hydantoin+IPBC, Emulsifier, Fragrance, Lanolin, Neatsfoot Oil

WARNINGS

Caution: If conditions persist or become worse, or in case of deep wounds, or serious burns, consult your veterinarian

For external use only.

For veterinary use only.

Keep out of the reach of children.

INDICATIONS AND USAGE

For horses and other animals: as soothing protection for chapped, windburned face and muzzle; as an emollient for minor irritations, abrasions, and burns; as a hoof hointment, helping maintain hoof health, moisture balance, supplenss.

For veterinary use only.

DESCRIPTION

For questions or comments

Call 1-800-690-9908 or visit www.mannapro.com